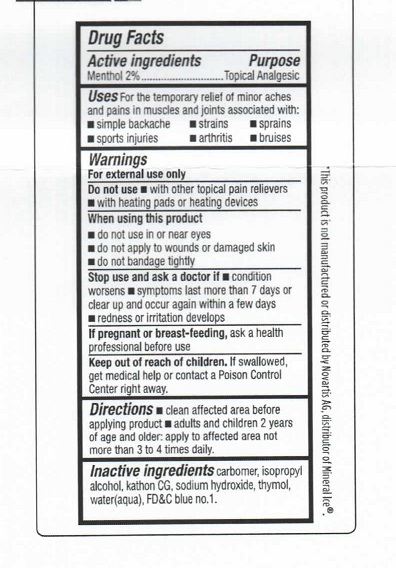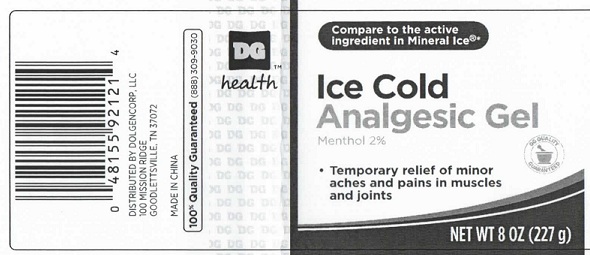 DRUG LABEL: DG Ice Cold Analgesic
                        
NDC: 55910-815 | Form: GEL
Manufacturer: Dolgencorp, LLC
Category: otc | Type: HUMAN OTC DRUG LABEL
Date: 20111123

ACTIVE INGREDIENTS: MENTHOL 2 g/100 g
INACTIVE INGREDIENTS: SODIUM HYDROXIDE; ISOPROPYL ALCOHOL; THYMOL; WATER

DG Health Ice Cold Analgesic Gel

Active Ingredient

Menthol (2%)

Purpose

Topical Analgesic

Uses

Uses-For the temporary relief of minor aches and pains in muscles and joints associated with:

simple backache

sports injuries

strains

arthritis

sprains

bruises

Warnings

For external use only

Do not use with other topical pain relievers

with heating pads or heating devices

When using this product

do not use in or near eyes

do not apply to wounds or damaged skin

do not bandage tightly

Stop use and ask a doctor if

condition worsens

symptoms last more than 7 days or clear up and occur again within a few days

redness or irritation develops

PREGNANCY OR BREAST FEEDING

If pregnant or breast-feeding, ask a health professional before use

Keep out of reach of children

If swallowed, get medical help or contact a poison control center right away.

Directions

Clean affected area before applying product

adults and children 2 years of age and older: apply to affected area not more than 3 to 4 times daily.

Inactive Ingredients

carbomer, isopropyl alcohol, kathon CG, sodium hydroxide, thymol, water(aqua), FDandC blue no 1

PACKAGE LABEL

Distributed by Dolgencorp, LLC
100 Mission Ridge
Goodlettsville, TN 37072
MADE IN CHINA
100% quality guaranteed
(888) 309-9030